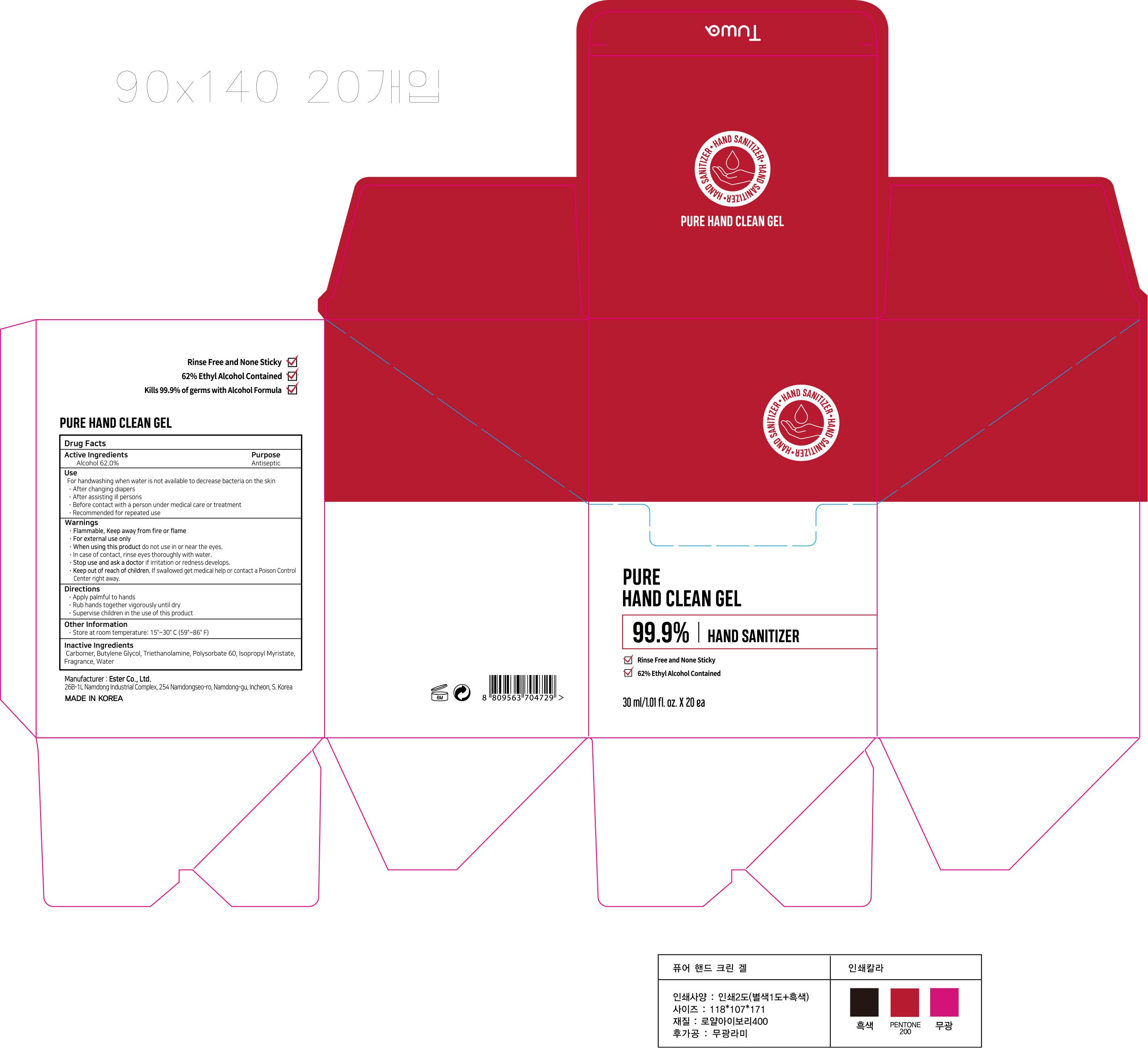 DRUG LABEL: PURE HAND CLEAN Gel
NDC: 74004-132 | Form: GEL
Manufacturer: Ester Co., Ltd.
Category: otc | Type: HUMAN OTC DRUG LABEL
Date: 20200417

ACTIVE INGREDIENTS: ALCOHOL 18.6 mL/30 mL
INACTIVE INGREDIENTS: POLYSORBATE 60; BUTYLENE GLYCOL; ISOPROPYL MYRISTATE; CARBOMER HOMOPOLYMER, UNSPECIFIED TYPE; WATER; TROLAMINE

[Ester Co., Ltd.-PURE HAND CLEAN Gel] 30 ml X 20 : 74004-132-20